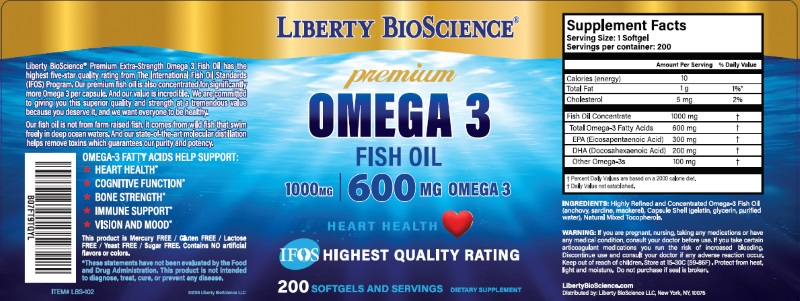 DRUG LABEL: Premium Omega 3
NDC: 71410-200 | Form: CAPSULE, GELATIN COATED
Manufacturer: Liberty Bioscience LLC
Category: other | Type: DIETARY SUPPLEMENT
Date: 20181001

ACTIVE INGREDIENTS: Icosapent 300 mg/1 1; Doconexent 200 mg/1 1; FISH OIL 1000 mg/1 1
INACTIVE INGREDIENTS: Gelatin; glycerin; tocopherol; mackerel, unspecified; sardine, unspecified; anchovy, unspecified

Premium Omega 3™

Supplement Facts

Dietary Supplement

Serving Size: 1 Softgel

Servings Per Container: 200

 | Amount Per Serving | % Daily Value
Calories | 10
Calories from Fat | 10
Total Fat | 1 g | 2% [Percent Daily Values are based on a 2,000 calorie diet.]
Saturated Fat | 0.5 g | 3%
Fish body oil EPA (eicosapentaenoic acid) 300 mg DHA (docosahexaenoic acid) 200 mg | 1,000 mg | [Daily value not established.]

Other ingredients: Gelatin, glycerin, Purified Water

Contains fish (mackerel, sardines, anchovy)

Warning

If you are pregnant, nursing, taking any medications or have any medical condition, consult your doctor before use.

SAFE HANDLING WARNING

- Keep out of the reach of children.
- Store at 15-30°C (59-86°F).
- Protect from heat, light and moisture.
- Do not purchase if seal is broken.

Distributed By:
Liberty BioScience™
New York, NY, 10075

HEALTH CLAIM

Help Support: Heart Healh, Cognitive Function, Bone Strength, Immune support, Vision and Mood.

This product is Mercury Free, Gluten Free, Lactose Free, Yeast Free, Sugar Free.

Contains NO artificial flavors or colors.

PRINCIPAL DISPLAY PANEL - 200 Capsule Bottle Label

Premium OMEGA 3™

EPA 300 / DHA 200 FORMULA

200 Softgels

Dietary Supplement